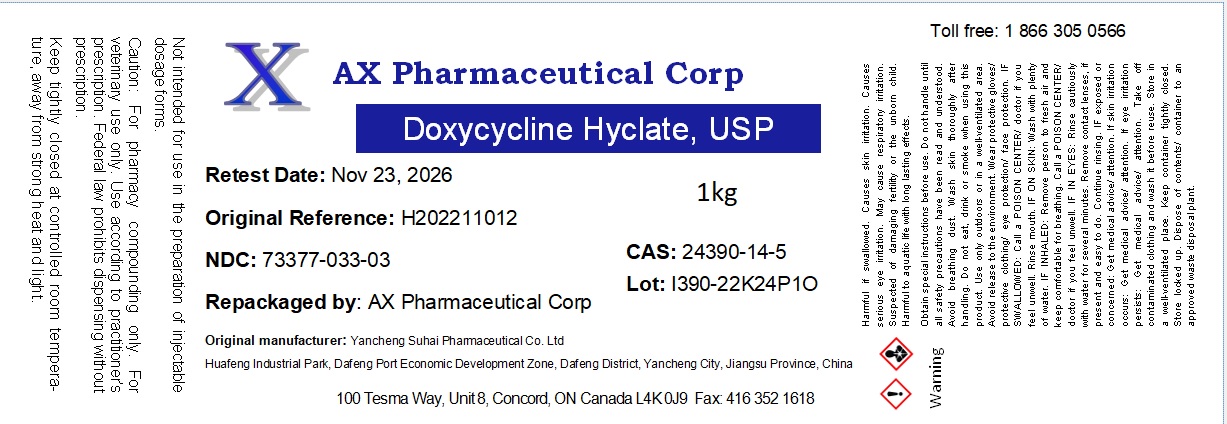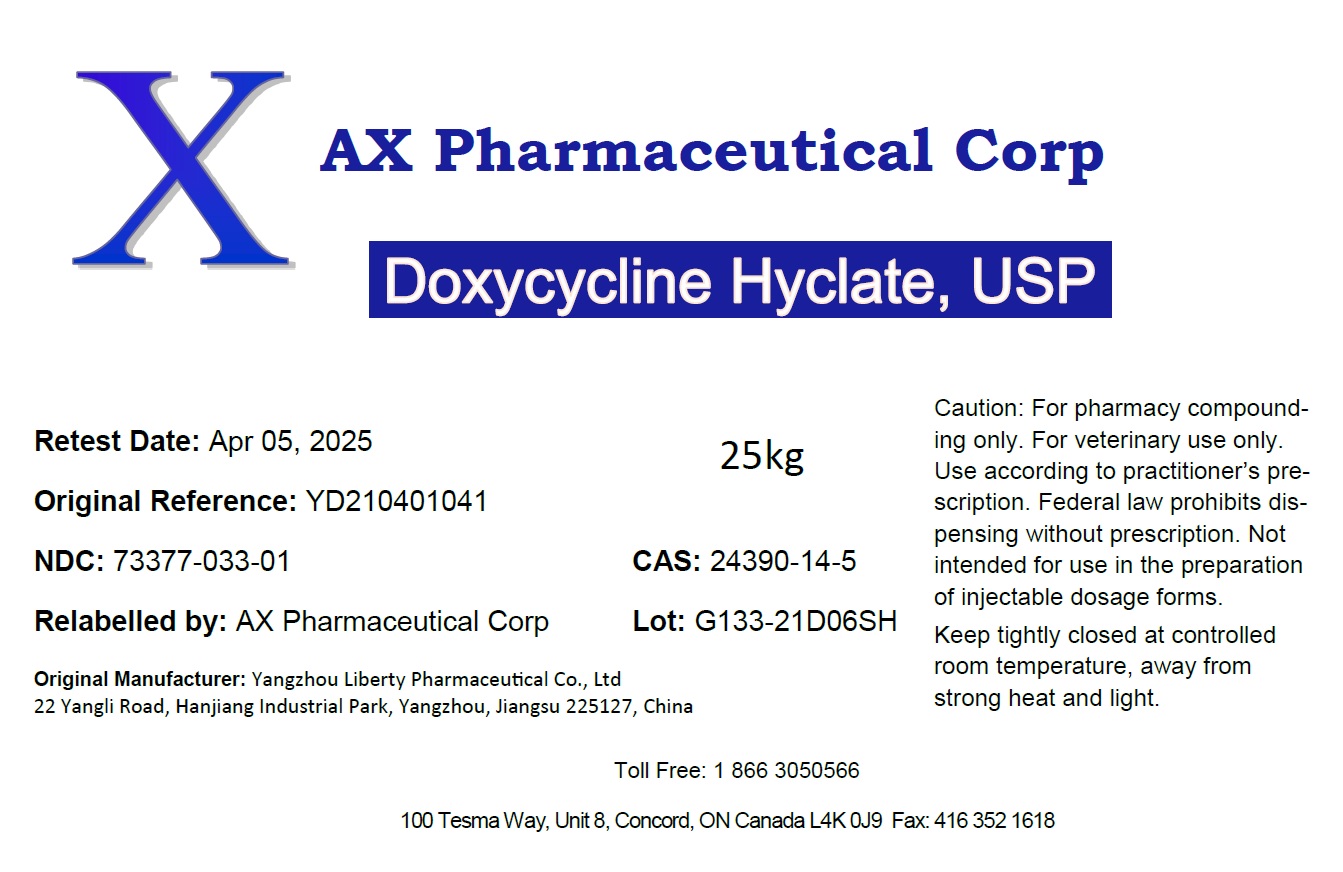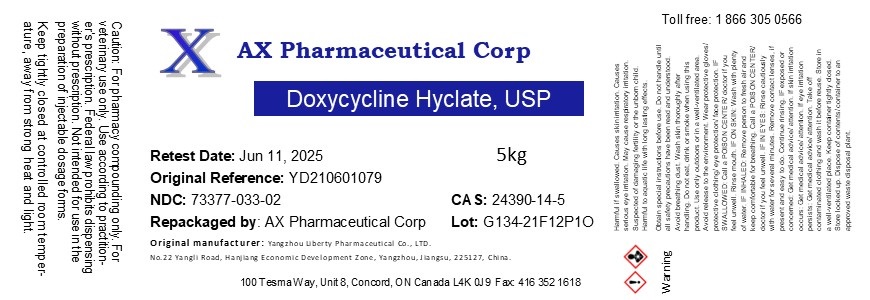 DRUG LABEL: Doxycycline Hyclate
NDC: 73377-033 | Form: POWDER
Manufacturer: AX Pharmaceutical Corp
Category: other | Type: BULK INGREDIENT - ANIMAL DRUG
Date: 20260209

ACTIVE INGREDIENTS: DOXYCYCLINE HYCLATE 1 kg/1 kg

Doxycycline Hyclate